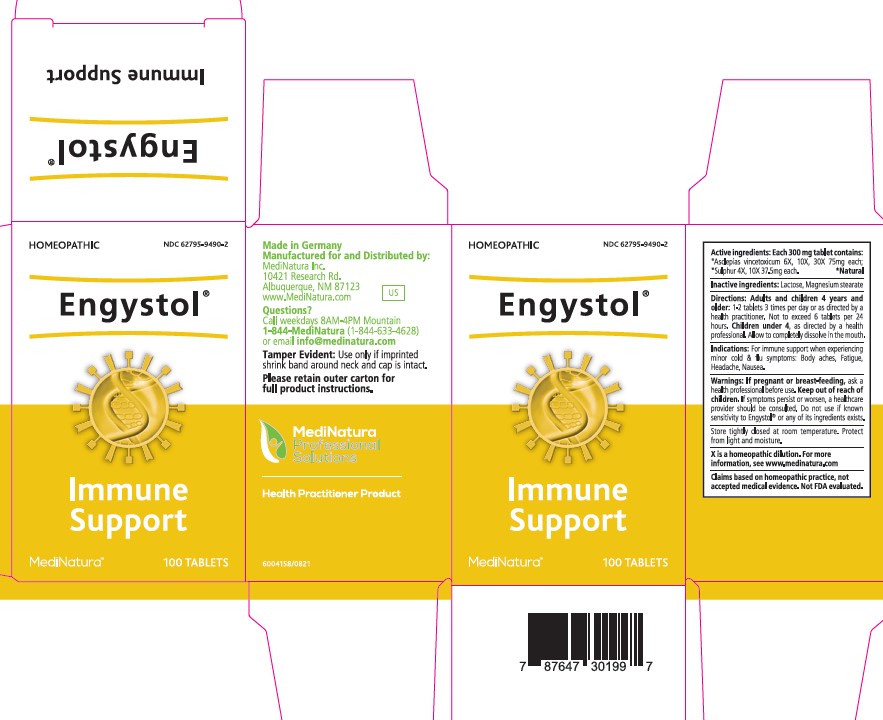 DRUG LABEL: Engystol
NDC: 62795-9490 | Form: TABLET
Manufacturer: Medinatura Inc
Category: homeopathic | Type: HUMAN OTC DRUG LABEL
Date: 20230927

ACTIVE INGREDIENTS: VINCETOXICUM HIRUNDINARIA ROOT 30 [hp_X]/1 1; SULFUR 10 [hp_X]/1 1
INACTIVE INGREDIENTS: MAGNESIUM STEARATE; LACTOSE, UNSPECIFIED FORM

Engystol

INDICATIONS & USAGE SECTION

For immune support when experiencing
minor cold & flu symptoms: Body aches, Fatigue,
Headache, Nausea.

Directions

Adults and children 4 years and
older: 1-2 tablets 3 times per day or as directed by a
health practitioner. Not to exceed 6 tablets per 24
hours. Children under 4, as directed by a health
professional. Allow to completely dissolve in the mouth.

Warnings:

If pregnant or breast-feeding, ask a
health professional before use. Keep out of reach of
children. If symptoms persist or worsen, a healthcare
provider should be consulted. Do not use if known
sensitivity to Engystol® or any of its ingredients exists.

Active ingredients:

Each 300 mg tablet contains:
*Asclepias vincetoxicum 6X, 10X, 30X 75mg each;
*Sulphur 4X, 10X 37.5mg each. *Natural

Inactive ingredients:

Lactose, Magnesium stearate

PURPOSE

Immune
Support

KEEP OUT OF REACH OF CHILDREN